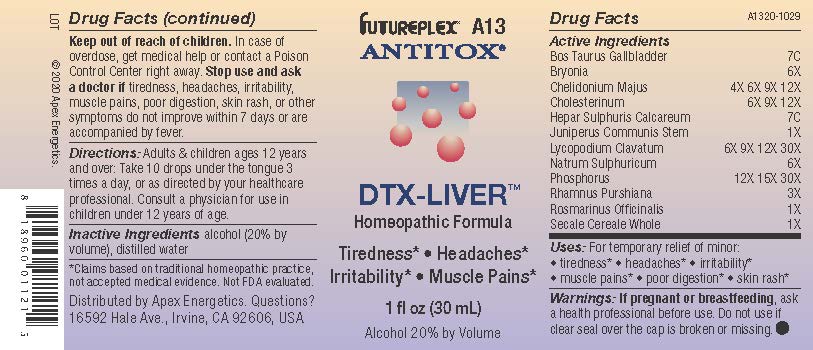 DRUG LABEL: A13
NDC: 63479-0113 | Form: SOLUTION/ DROPS
Manufacturer: Apex Energetics Inc.
Category: homeopathic | Type: HUMAN OTC DRUG LABEL
Date: 20240108

ACTIVE INGREDIENTS: BRYONIA ALBA ROOT 6 [hp_X]/1 mL; PHOSPHORUS 30 [hp_X]/1 mL; BOS TAURUS GALLBLADDER 7 [hp_C]/1 mL; CALCIUM SULFIDE 7 [hp_C]/1 mL; JUNIPERUS COMMUNIS STEM 1 [hp_X]/1 mL; SECALE CEREALE WHOLE 1 [hp_X]/1 mL; SODIUM SULFATE 6 [hp_X]/1 mL; FRANGULA PURSHIANA BARK 3 [hp_X]/1 mL; ROSMARINUS OFFICINALIS FLOWERING TOP 1 [hp_X]/1 mL; CHELIDONIUM MAJUS 12 [hp_X]/1 mL; CHOLESTEROL 12 [hp_X]/1 mL; LYCOPODIUM CLAVATUM SPORE 30 [hp_X]/1 mL
INACTIVE INGREDIENTS: ALCOHOL; WATER

A13

Active Ingredients
Bos Taurus Gallbladder | 7C
Bryonia | 6X
Chelidonium Majus | 4X 6X 9X 12X
Cholesterinum | 6X 9X 12X
Hepar Sulphuris Calcareum | 7C
Juniperus Communis Stem | 1X
Lycopodium Clavatum | 6X 9X 12X 30X
Natrum Sulphuricum | 6X
Phosphorus | 12X 15X 30X
Rhamnus Purshiana | 3X
Rosmarinus Officinalis | 1X
Secale Cereale Whole | 1X

INDICATIONS AND USAGE

Uses:

For temporary relief of minor: •

tiredness*

headaches*

irritability*

muscle pains*

poor digestion*

skin rash*

*Claims based on traditional homeopathic practice, not accepted medical evidence. Not FDA evaluated.

Warnings:

PREGNANCY OR BREAST FEEDING

If pregnant or breastfeeding, ask a health professional before use.

Do not use if clear seal over the cap is broken or missing.

Keep out of reach of children. In case of overdose, get medical help or contact a Poison Control Center right away.

Stop use and ask a doctor if tiredness, headaches, irritability, muscle pains, poor digestion, skin rash, or other symptoms do not improve within 7 days or are accompanied by fever.

Directions:

Adults & children ages 12 years and over: Take 10 drops under the tongue 3 times a day, or as directed by your healthcare professional. Consult a physician for use in children under 12 years of age.

Inactive Ingredients

alcohol (20% by volume), distilled water

Distributed by Apex Energetics. Questions?

16592 Hale Ave., Irvine, CA 92606, USA

PACKAGE LABEL

FUTUREPLEX® A13

ANTITOX®

DTX-LIVER™

Homeopathic Formula

Tiredness*

Headaches*

Irritability*

Muscle Pains*

1 fl oz (30 mL)

Alcohol 20% by Volume